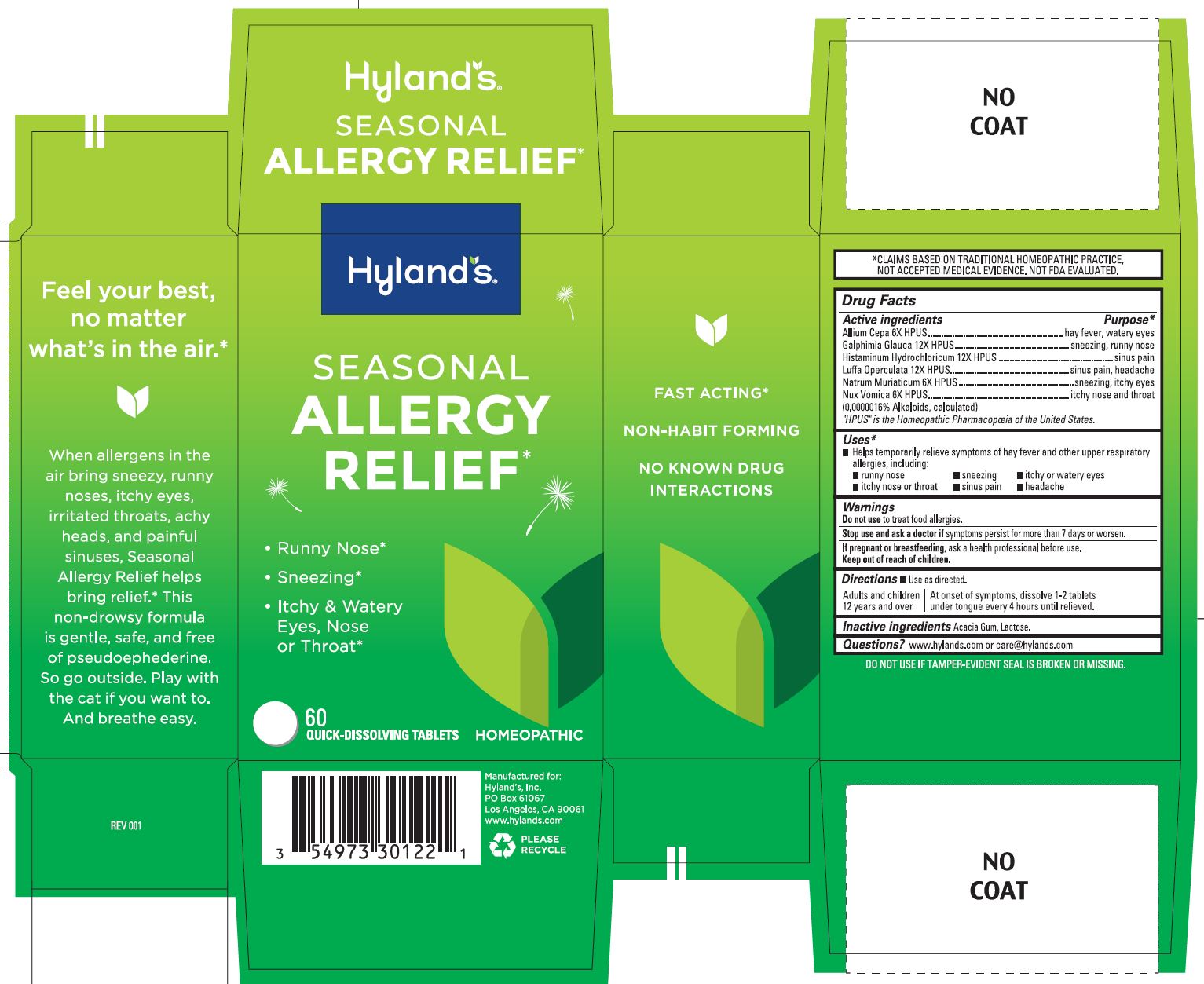 DRUG LABEL: Seasonal Allergy Relief
NDC: 54973-3012 | Form: TABLET, SOLUBLE
Manufacturer: Hyland's Inc.
Category: homeopathic | Type: HUMAN OTC DRUG LABEL
Date: 20250430

ACTIVE INGREDIENTS: ONION 6 [hp_X]/1 1; SODIUM CHLORIDE 6 [hp_X]/1 1; HISTAMINE DIHYDROCHLORIDE 12 [hp_X]/1 1; CUCUMBER 12 [hp_X]/1 1; GALPHIMIA GLAUCA FLOWERING TOP 12 [hp_X]/1 1; STRYCHNOS NUX-VOMICA SEED 6 [hp_X]/1 1
INACTIVE INGREDIENTS: ACACIA; LACTOSE

Hyland's Seasonal Allergy Relief

PURPOSE

Relieves Runny Nose, Sneezing, Itchy or Watery Eyes, Nose or Throat

Drug Facts

Active Ingredients | Purpose
Allium Cepa 6X HPUS | hay fever, watery eyes
Galphimia Glauca 12X HPUS | sneezing, runny nose
Histaminum Hydrochloricum 12X HPUS | sinus pain
Luffa Operculata 12X HPUS | sinus pain, headache
Natrum Muriaticum 6X HPUS | sneezing, itchy eyes
Nux Vomica 6X HPUS (0.0000016% Alkaloids, calculated) | itchy nose & throat

"HPUS" indicates the active ingredients are offiacial Homeopathic Pharmacopœia of the United States.

Uses

■ Temporarily relieves symptoms of hay fever and other upper respiratory allergies, including:

■ runny nose ■ sneezing ■ itchy or watery eyes
■ itchy nose or throat ■ sinus pain ■ headache

Warnings

Do not use

to treat food allergies.

Stop use and ask a doctor if

symptoms persist for more than 7 days or worsen.

If pregnant or breastfeeding

ask a health professional before use.

Directions

■ Use as directed.

Adults and children
12 years and over

At onset of symptoms, dissolve 1-2 tablets
under tongue every 4 hours until relieved

Inactive Ingredients

Acacia Gum, Lactose.

Questions?

www.hylands.com or care@hylands.com

Indications and Usage

Uses Changed to ■ Temporarily relieves symptoms of hay fever and other upper respiratory allergies, including: ■ runny nose ■ sneezing ■ itchy or watery eyes ■ itchy nose or throat ■ sinus pain ■ headache

Dosage and Administration

Directions Adults and children 12 years and over: Dissolve 1-2 tablets
under tongue every 4 hours until relieved.

05/09/2022 - Updates

Directions

■ Use as directed.

Adults and children
12 years and over

At onset of symptoms, dissolve 1-2 tablets
under tongue every 4 hours until relieved.

PRINCIPAL DISPLAY PANEL

Hyland's

NATURALS™

SEASONAL

ALLERGY

RELIEF*

• Runny Nose

• Sneezing

• Itchy & Watery

Eyes, Nose

or Throat

60

QUICK-DISSOLVING TABLETS

HOMEOPATHIC